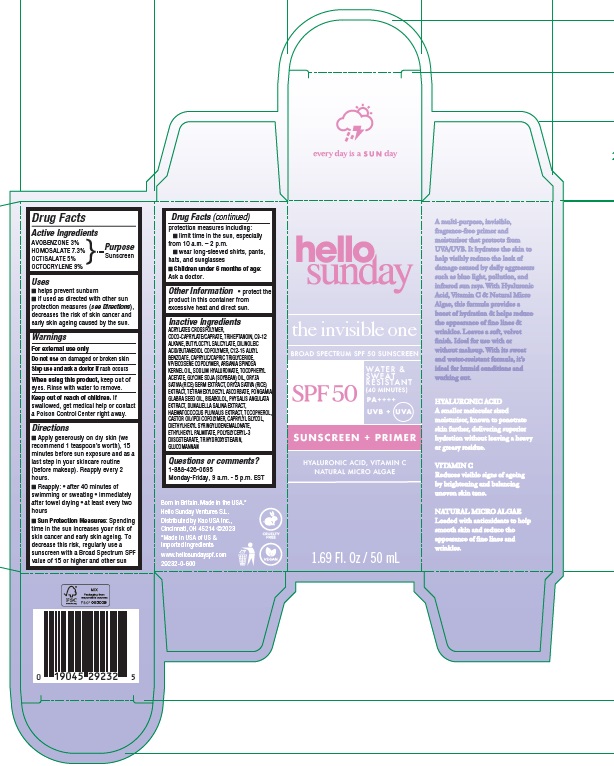 DRUG LABEL: Hello Sunday The Invisible One Sunscreen Plus Primer SPF 50
NDC: 10596-801 | Form: EMULSION
Manufacturer: Kao USA Inc.
Category: otc | Type: HUMAN OTC DRUG LABEL
Date: 20250131

ACTIVE INGREDIENTS: OCTISALATE 50 mg/1 mL; OCTOCRYLENE 90 mg/1 mL; HOMOSALATE 73 mg/1 mL; AVOBENZONE 30 mg/1 mL
INACTIVE INGREDIENTS: TRIHEPTANOIN; HYALURONATE SODIUM; RICE GERM; KARUM SEED OIL; TRIHYDROXYSTEARIN; TETRAHEXYLDECYL ASCORBATE; HAEMATOCOCCUS PLUVIALIS; BUTYLOCTYL SALICYLATE; DILINOLEIC ACID/BUTANEDIOL COPOLYMER; ARGAN OIL; TOCOPHEROL; DIETHYLHEXYL SYRINGYLIDENEMALONATE; ALKYL (C12-15) BENZOATE; VINYLPYRROLIDONE/EICOSENE COPOLYMER; ALPHA-TOCOPHEROL ACETATE; DUNALIELLA SALINA; ETHYLHEXYL PALMITATE; LEVOMENOL; KONJAC MANNAN; PHYSALIS ANGULATA WHOLE; CAPRYLYL GLYCOL; C9-12 ALKANE; POLYGLYCERYL-3 DIISOSTEARATE; COCO-CAPRYLATE/CAPRATE; MEDIUM-CHAIN TRIGLYCERIDES; SOYBEAN OIL

Hello Sunday The Invisible One Sunscreen Plus Primer SPF 50

Active Ingredients

AVOBENZONE 3%
HOMOSALATE 7.3%
OCTISALATE 5%
OCTOCRYLENE 9%

Purpose

Sunscreen

Uses

- helps prevent sunburn
- if used as directed with other sun protection measures (see Directions), decreases the risk of skin cancer and early skin ageing caused by the sun.

Warnings

For external use only

Do not use

on damaged or broken skin

Stop use and ask a doctor if

rash occurs

When using this product

keep out of eyes. Rinse with water to remove.

Keep out of reach of children.

If swallowed, get medical help or contact a Poison Control Center right away.

Directions

- Apply generously on dry skin (we recommend 1 teaspoon’s worth), 15 minutes before sun exposure and as a last step in your skincare routine (before makeup). Reapply every 2 hours.
- Reapply:
- after 40 minutes of swimming or sweating
- immediately after towel drying
- at least every two hours
- Sun Protection Measures: Spending time in the sun increases your risk of skin cancer and early skin ageing. To decrease this risk, regularly use a sunscreen with a Broad Spectrum SPF value of 15 or higher and other sun protection measures including:
- limit time in the sun, especially from 10 a.m. – 2 p.m.
- wear long-sleeved shirts, pants, hats, and sunglasses
- Children under 6 months of age: Ask a doctor.

Other Information

- protect the product in this container from excessive heat and direct sun.

Inactive Ingredients

ACRYLATES CROSSPOLYMER, COCO-CAPRYLATE/CAPRATE, TRIHEPTANOIN, C9-12 ALKANE, BUTYLOCTYL SALICYLATE, DILINOLEIC ACID/BUTANEDIOL COPOLYMER, C12-15 ALKYL BENZOATE, CAPRYLIC/CAPRIC TRIGLYCERIDE, VP/EICOSENE COPOLYMER, ARGANIA SPINOSA KERNEL OIL, SODIUM HYALURONATE, TOCOPHERYL ACETATE, GLYCINE SOJA (SOYBEAN) OIL, ORYZA SATIVA (RICE) GERM EXTRACT, ORYZA SATIVA (RICE) EXTRACT, TETRAHEXYLDECYL ASCORBATE, PONGAMIA GLABRA SEED OIL, BISABOLOL, PHYSALIS ANGULATA EXTRACT, DUNALIELLA SALINA EXTRACT, HAEMATOCOCCUS PLUVIALIS EXTRACT, TOCOPHEROL, CASTOR OIL/IPDI COPOLYMER, CAPRYLYL GLYCOL, DIETHYLHEXYL SYRINGYLIDENEMALONATE, ETHYLHEXYL PALMITATE, POLYGLYCERYL-3 DIISOSTEARATE, TRIHYDROXYSTEARIN, GLUCOMANNAN

Questions or comments?

1-888-426-0695
Monday-Friday, 9 a.m. - 5 p.m. EST